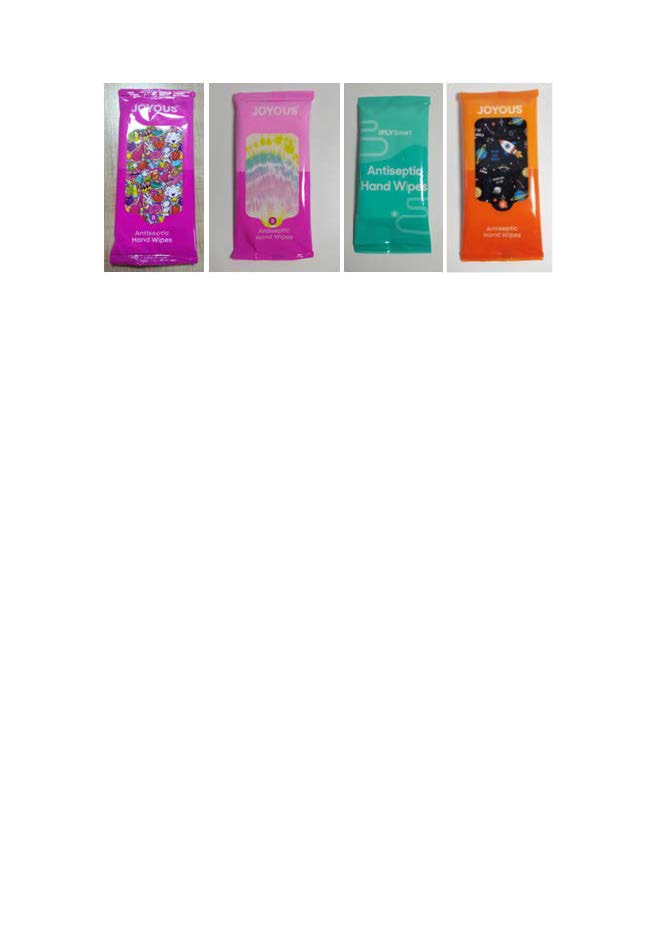 DRUG LABEL: Hand Wipes
NDC: 75111-601 | Form: CLOTH
Manufacturer: Enping Jiaxin Daily Necessities Co., Ltd.
Category: otc | Type: HUMAN OTC DRUG LABEL
Date: 20200907

ACTIVE INGREDIENTS: BENZALKONIUM CHLORIDE 0.13 1/100 1
INACTIVE INGREDIENTS: PROPYLENE GLYCOL; ALOE VERA LEAF; DECYL GLUCOSIDE; POLYSORBATE 20; GLYCERIN; POLYAMINOPROPYL BIGUANIDE; WATER; CETYLPYRIDINIUM CHLORIDE

Hand Wipes

Active Ingredient(s)

Benzalkonium chloride 0.13%. Purpose: Antiseptic

Purpose

Antiseptic, Hand Wipes

Use

Hand Wipes to help reduce bacteria that potentially can cause disease. For use when soap and water are not available.

Warnings

For external use only. Flammable. Keep away from heat or flame

Do not use

- in children less than 2 months of age
- on open skin wounds

When using this product keep out of eyes, ears, and mouth. In case of contact with eyes, rinse eyes thoroughly with water.
Stop use and ask a doctor if irritation or rash occurs. These may be signs of a serious condition.
Keep out of reach of children. If swallowed, get medical help or contact a Poison Control Center right away.

Stop use and ask a doctor if irritation or rash occurs. These may be signs of a serious condition.

Keep out of reach of children. If swallowed, get medical help or contact a Poison Control Center right away.

Directions

- Wipe the body skin or other suiface.
- Supervise children under 6 years of age when using this product to avoid swallowing.

Other information

- Store between 15-30C (59-86F)
- Avoid freezing and excessive heat above 40C (104F)

Inactive ingredients

Glycerin;

Polyaminopropyl Biguanide;

Propylene Glycol;

Aloe Barbadensis Leaf Juice;

Decyl glucoside;

Polysorbate 20;

Cetylpyridinium Chloride;

Water.